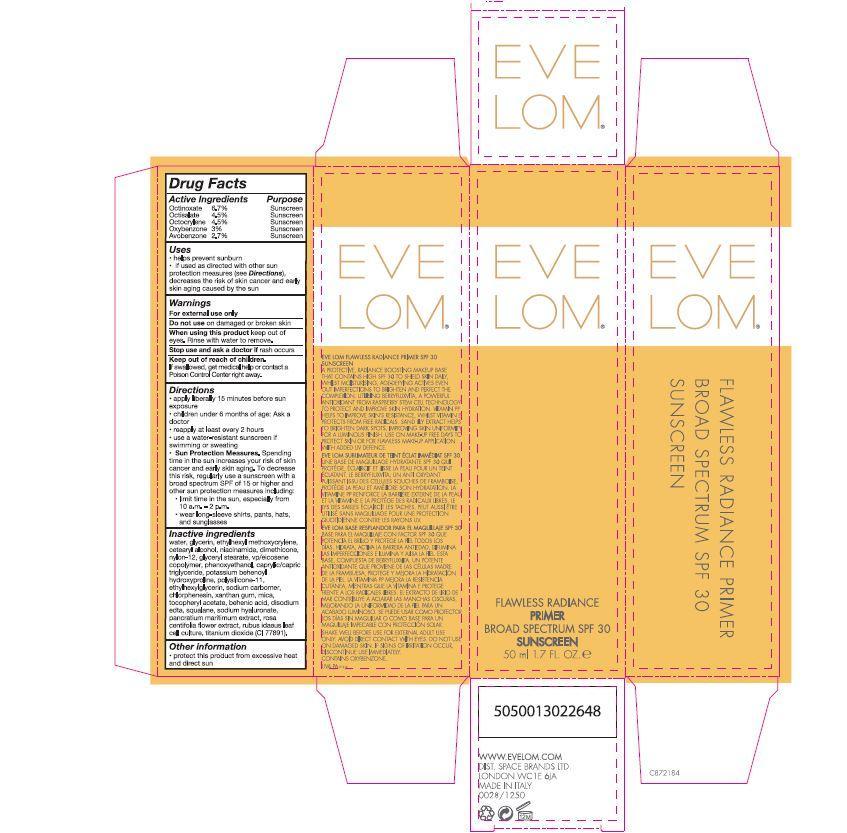 DRUG LABEL: Eve Lom Flawless Radiance Primer Broad Spectrum SPF 30 Sunscreen
NDC: 61601-1250 | Form: LOTION
Manufacturer: Space Brands Limited
Category: otc | Type: HUMAN OTC DRUG LABEL
Date: 20141114

ACTIVE INGREDIENTS: OCTINOXATE 3.35 g/50 mL; OCTISALATE 2.25 g/50 mL; OCTOCRYLENE 2.25 g/50 mL; OXYBENZONE 1.50 g/50 mL; AVOBENZONE 1.35 g/50 mL
INACTIVE INGREDIENTS: WATER; GLYCERIN; ETHYLHEXYL METHOXYCRYLENE; CETOSTEARYL ALCOHOL; NIACINAMIDE; DIMETHICONE; NYLON-12; GLYCERYL MONOSTEARATE; VINYLPYRROLIDONE/EICOSENE COPOLYMER; PHENOXYETHANOL; MEDIUM-CHAIN TRIGLYCERIDES; POTASSIUM BEHENOYL HYDROXYPROLINE; ETHYLHEXYLGLYCERIN; CHLORPHENESIN; XANTHAN GUM; MICA; .ALPHA.-TOCOPHEROL ACETATE; BEHENIC ACID; EDETATE DISODIUM; SQUALANE; TITANIUM DIOXIDE; HYALURONATE SODIUM; ROSA CENTIFOLIA FLOWER

Eve Lom® Flawless Radiance Primer Broad Spectrum SPF 30 Sunscreen

Drug Facts

Active Ingredients Purpose

Octinoxate 6.7% Sunscreen

Octisalate 4.5% Sunscreen

Octocrylene 4.5% Sunscreen

Oxybenzone 3% Sunscreen

Avobenzone 2.7% Sunscreen

Uses

- helps prevent sunburn
- if used as directed with other sun protection measures (see Directions), decreases the risk of skin cancer and early skin aging caused by the sun

Warnings

For external use only

Do not use on damaged or broken skin

When using this product keep out of eyes. Rinse with water to remove.

Stop use and ask a doctor if rash occurs.

Keep out of reach of children.

If swallowed, get medical help or contact a Poison Control Center right away.

Directions

- apply liberally 15 minutes before sun exposure
- children under 6 months of age: Ask a doctor
- reapply at least every 2 hours
- use a water-resistant sunscreen if swimming or sweating
- Sun Protection Measures. Spending time in the sun increases your risk of skin cancer and early skin aging. To decrease this risk, regularly use a sunscreen with a broad spectrum SPF of 15 of higher and other sun protection measures including:

- limit time in the sun, especially from 10 a.m. - 2 p.m.

- wear long-sleeve shirts, pants, hats, and sunglasses

Inactive ingredients

water, glycerin, ethylhexyl methoxycrylene, cetearyl alcohol, niacinamide, dimethicone, nylon-12, glyceryl stearate, vp/eicosene copolymer, phenoxyethanol, caprylic/capric triglyceride, potassium behenoyl hydroxyproline, polysilicone-11, ethylhexylhlycerin, sodium carbomer, chlorphenesin, xanthan gum, mica, tocopheryl acetate, behenic acid, disodium edta, squalane, sodium hyaluronate, pancratium maritimum extract, rosa centifolia flower extract, rubus idaeus leaf cell culture, titanium dioxide (CI 77891).

Other information

- protect this product from excessive heat and direct sun